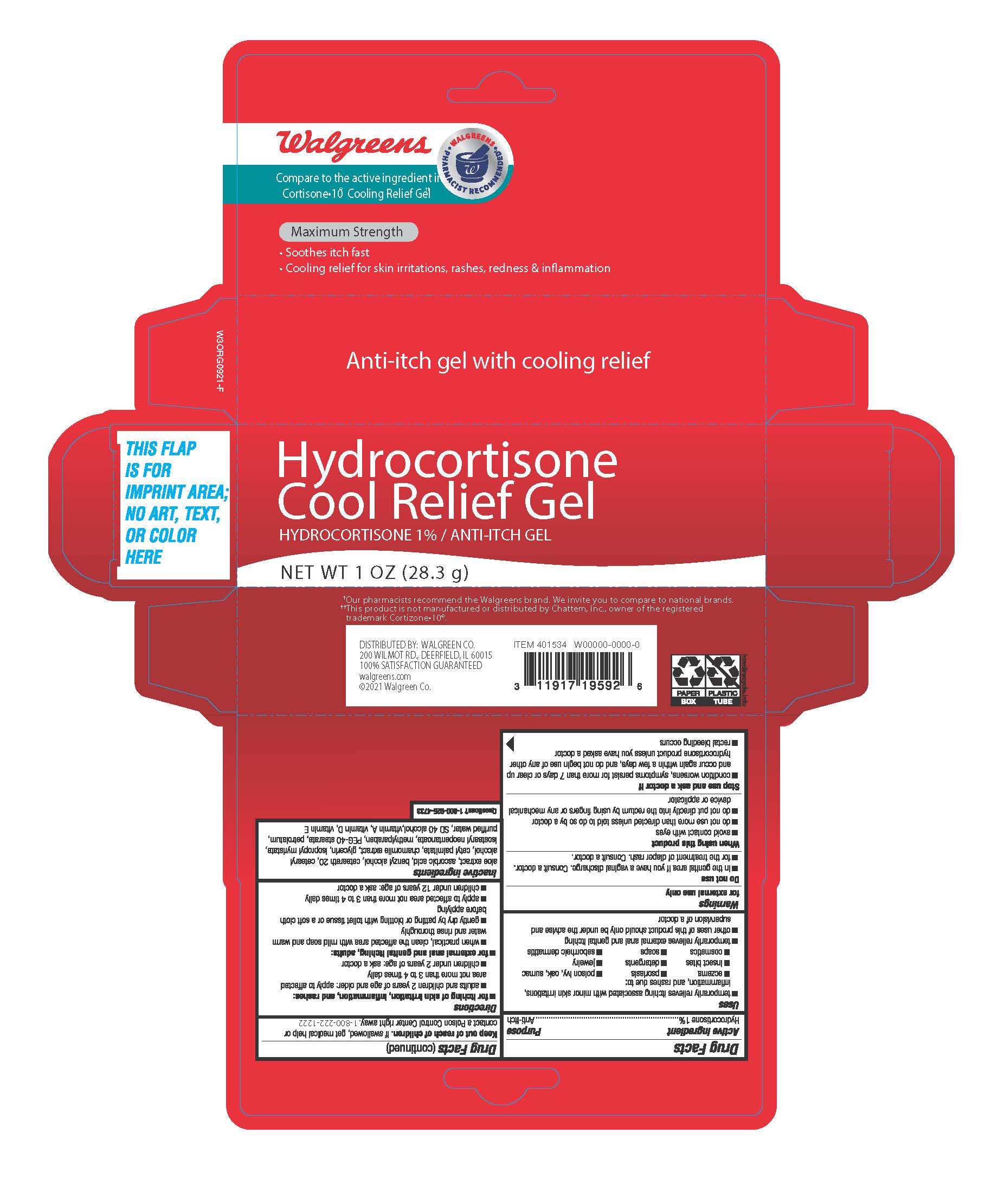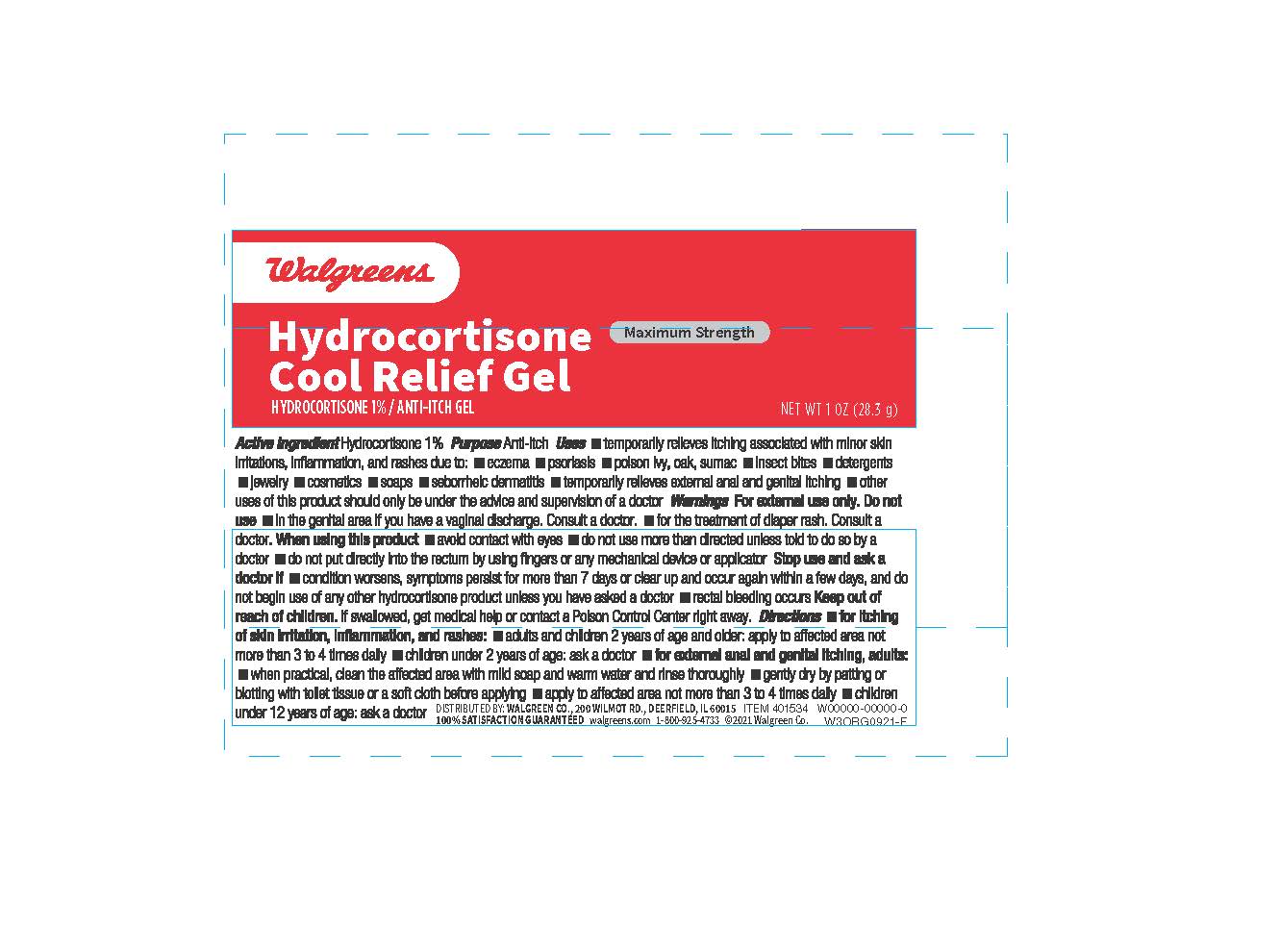 DRUG LABEL: Hydrocortisone
NDC: 0363-0363 | Form: GEL
Manufacturer: Walgreens
Category: otc | Type: HUMAN OTC DRUG LABEL
Date: 20260114

ACTIVE INGREDIENTS: HYDROCORTISONE 1 g/100 g
INACTIVE INGREDIENTS: ANHYDROUS TRISODIUM CITRATE; DIMETHICONE; METHYL LACTATE, L-; METHYL GLUCETH-20; PPG-3 BENZYL ETHER MYRISTATE; ALCOHOL; HYDROXYETHYL ACRYLATE/SODIUM ACRYLOYLDIMETHYL TAURATE COPOLYMER (45000 MPA.S AT 1%); MALTODEXTRIN; OAT; WATER; ALOE VERA LEAF; EDETATE DISODIUM; ICODEXTRIN; POLYSORBATE 60; PROPYLPARABEN; ISOHEXADECANE; METHYLPARABEN; GLYCERIN

Walgreens Hydrocortisone Cool Relief Gel

Drug Facts

Active Ingredients

Hydrocortisone 1%

Drug Facts

Purpose : Anti-itch

Drug Facts

Uses:

■ temporarily relieves itching associated with minor skin irritations, inflammation and rashes due to: ■ eczema ■ psoriasis ■ poison ivy, oak and sumac ■insect bites ■ detergents ■ jewelry ■ cosmetics ■ soaps ■ seborrheic dermatitis ■ temporarily relieves external anal and genital itching ■ other uses of this product should oonly be under the advise and supervison of a doctor

Warnings: For external use only

Do not use

■ in the genital area if you have a vaginal discharge. Consult a doctor.

■ for the treatment of diaper rash. Consult a doctor.

When using this product

■ avoid contact with eyes ■ do not use more than directed unless told to do so by a doctor ■ do not put directly into the rectum by using fingers or any mechanical device or applicator

Stop use and ask a doctor if ■ condition worsens, symptoms persist for more than 7 days or clear up and occur again within a few days, and do not begin use of any other hydrocortisone product unless you have asked a doctor. ■ rectal bleeding occurs

Keep out of reach of children. If swallowed, get medical help or contact a Poison Control Center right away. 1-800-222-1222

Directions

Directions ■ for itching of skin irritation, inflammation, and rashes: ■ adults and children 2 years of age and older: apply to affected area not more than 3 to 4 times daily ■ children under 2 years of age: ask a doctor ■ If pregnant or breast-feeding: ask a health professional before use. ■ for external anal and genital itching, adults: ■ when practical, clean the affected area with mild soap and warm water and rinse thoroughly ■ gently dry by patting or blotting with toilet tissue or a soft cloth before applying ■ apply to affected area not more than 3 to 4 times daily ■ children under 12 years of age: ask a doctor

Inactive ingredients:

Aloe extract, ascorbic acid, benzyl alcohol, ceteareth 20, cetearyl alcohol, cetyl palmitate, chamomile extract, glycerin, isopropyl myristate, isostearyl neopentanoate, methylparaben, PEG-40 stearate, petrolatum, purified water, sd 40 alcohol, vitamin A, vitamin D and vitamin E

SAFE HANDLING WARNING

TAMPER EVIDENT DO NOT USE IF SEAL ON TUBE IS PUNCTURED OR MISSING